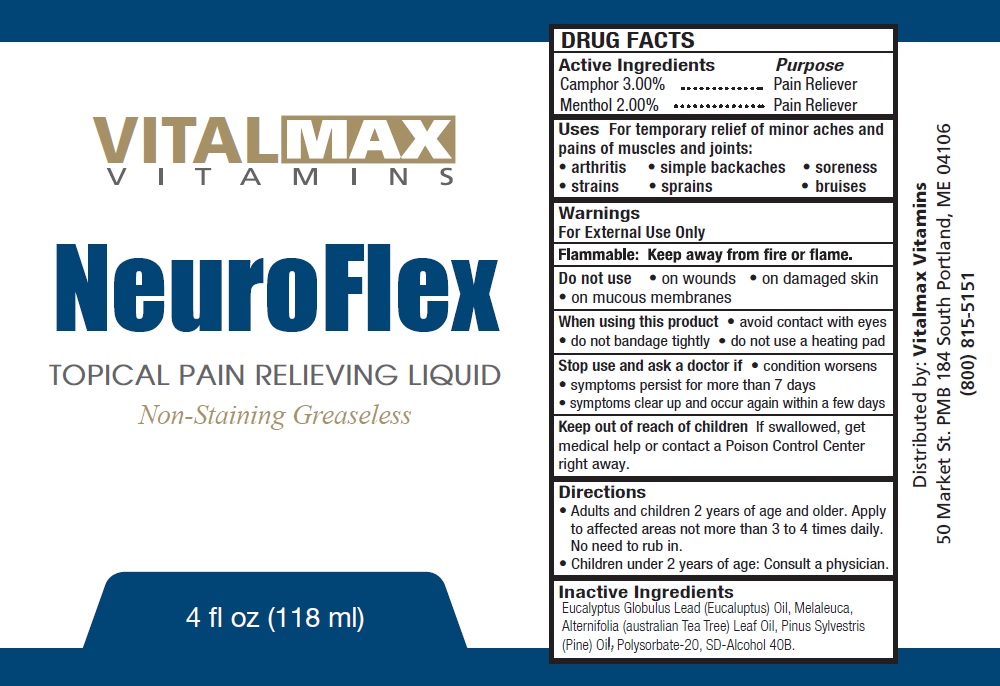 DRUG LABEL: NEUROFLEX Topical Pain Relieving Liquid
NDC: 69876-1740 | Form: SOLUTION
Manufacturer: Almark Products Inc
Category: otc | Type: HUMAN OTC DRUG LABEL
Date: 20231110

ACTIVE INGREDIENTS: CAMPHOR (SYNTHETIC) 30 mg/1 mL; MENTHOL 20 mg/1 mL
INACTIVE INGREDIENTS: EUCALYPTUS GUM; TEA TREE OIL; PINE NEEDLE OIL (PINUS SYLVESTRIS); POLYSORBATE 20

NEUROFLEX Topical Pain Relieving Liquid

Active Ingredients

Camphor 3.00% Menthol 2.00%

Purpose

Pain Reliever

Uses

For temporary relief of minor aches and pains of muscles and joints: • arthritis • simple backaches • soreness • strains • sprains • bruises

Warnings

For External Use Only

Flammable: Keep away from fire or flame.

Do not use

• on wounds • on damaged skin • on mucous membranes

When using this product

• avoid contact with eyes • do not bandage tightly • do not use a heating pad

Stop use and ask a doctor if

• condition worsens • symptoms persist for more than 7 days • symptoms clear up and occur again within a few days

Keep out of reach of children

If swallowed, get medical help or contact a Poison Control Center right away.

Directions

• Adults and children 2 years of age and older. Apply to affected areas not more than 3 to 4 times daily. No need to rub in. • Children under 2 years of age: Consult a physician.

Inactive Ingredients

Eucalyptus Globulus Lead (Eucaluptus) Oil, Melaleuca, Alternifolia (australian Tea Tree) Leaf Oil, Pinus Sylvestris (Pine) Oil, Polysorbate-20, SD-Alcohol 40B.